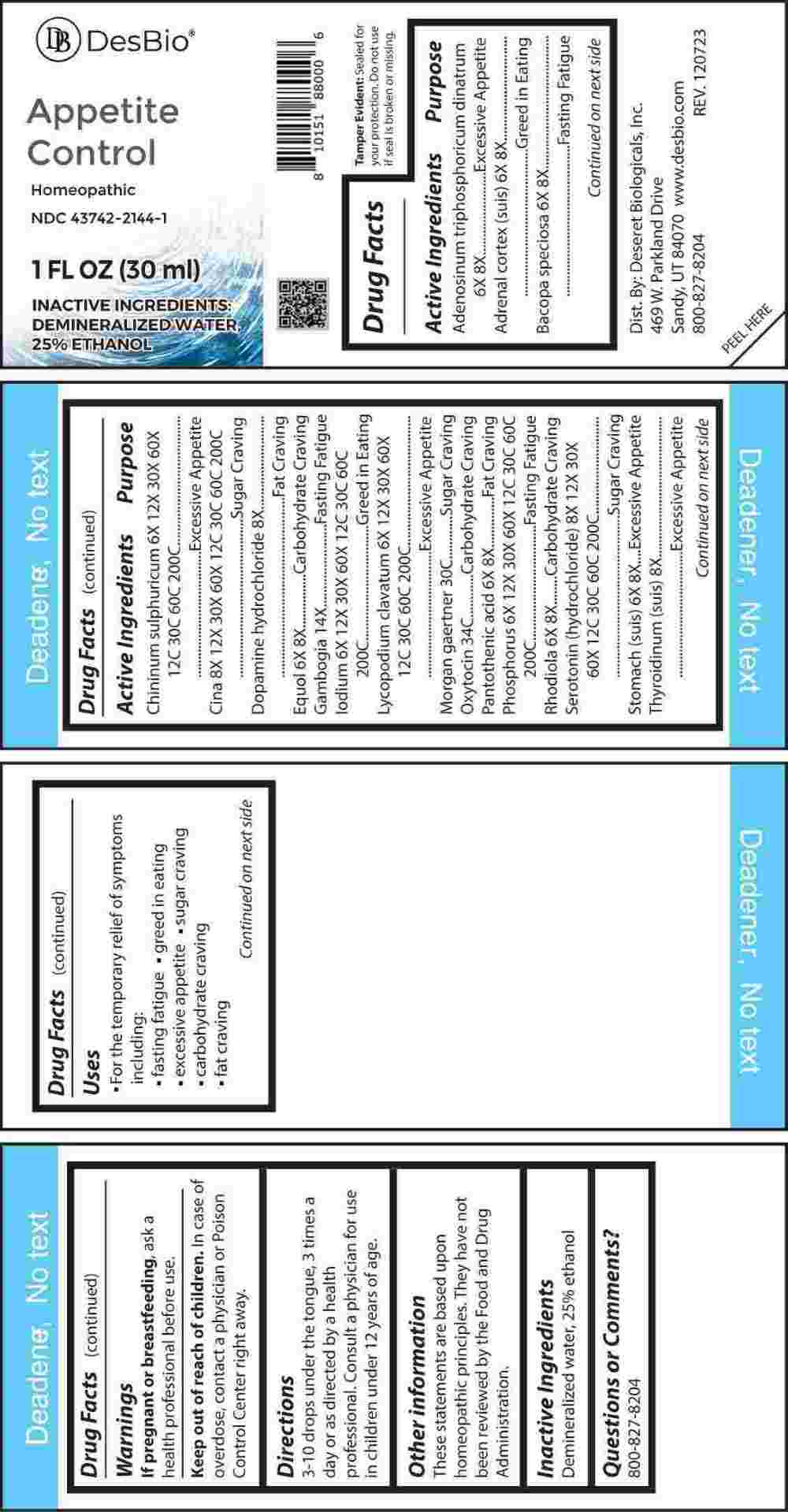 DRUG LABEL: Appetite Control
NDC: 43742-2144 | Form: LIQUID
Manufacturer: Deseret Biologicals, Inc.
Category: homeopathic | Type: HUMAN OTC DRUG LABEL
Date: 20240312

ACTIVE INGREDIENTS: ADENOSINE TRIPHOSPHATE DISODIUM 6 [hp_X]/1 mL; SUS SCROFA ADRENAL CORTEX 6 [hp_X]/1 mL; BACOPA MONNIERA LEAF 6 [hp_X]/1 mL; QUININE SULFATE 6 [hp_X]/1 mL; ARTEMISIA CINA PRE-FLOWERING TOP 8 [hp_X]/1 mL; DOPAMINE HYDROCHLORIDE 8 [hp_X]/1 mL; EQUOL 6 [hp_X]/1 mL; GAMBOGE 14 [hp_X]/1 mL; IODINE 6 [hp_X]/1 mL; LYCOPODIUM CLAVATUM SPORE 6 [hp_X]/1 mL; SALMONELLA ENTERICA ENTERICA SEROVAR ENTERITIDIS 30 [hp_C]/1 mL; OXYTOCIN 34 [hp_C]/1 mL; PANTOTHENIC ACID 6 [hp_X]/1 mL; PHOSPHORUS 6 [hp_X]/1 mL; SEDUM ROSEUM ROOT 6 [hp_X]/1 mL; SEROTONIN HYDROCHLORIDE 8 [hp_X]/1 mL; SUS SCROFA STOMACH 6 [hp_X]/1 mL; THYROID 8 [hp_X]/1 mL
INACTIVE INGREDIENTS: WATER; ALCOHOL

DRUG FACTS:

ACTIVE INGREDIENTS:

Adenosinum Triphosphoricum Dinatrum 6X, 8X, Adrenal Cortex (Suis) 6X, 8X, Bacopa Speciosa 6X, 8X, Chininum Sulphuricum 6X, 12X, 30X, 60X, 12C, 30C, 60C, 200C, Cina 8X, 12X, 30X, 60X, 12C, 30C, 60C, 200C, Dopamine Hydrochloride 8X, Equol 6X, 8X, Gambogia 14X, Iodium 6X, 12X, 30X, 60X, 12C, 30C, 60C, 200C, Lycopodium Clavatum 6X, 12X, 30X, 60X, 12C, 30C, 60C, 200C, Morgan Gaertner 30C, Oxytocin 34C, Pantothenic Acid 6X, 8X, Phosphorus 6X, 12X, 30X, 60X, 12C, 30C, 60C, 200C, Rhodiola 6X, 8X, Serotonin (Hydrochloride) 8X, 12X, 30X, 60X, 12C, 30C, 60C, 200C, Stomach (Suis) 6X, 8X, Thyroidinum (Suis) 8X.

PURPOSE:

Adenosinum Triphosphoricum Dinatrum – Excessive Appetite, Adrenal Cortex (Suis) – Greed in Eating, Bacopa Speciosa – Fasting Fatigue, Chininum Sulphuricum – Excessive Appetite, Cina – Sugar Craving, Dopamine Hydrochloride – Fat Craving, Equol – Carbohydrate Craving, Gambogia – Fasting Fatigue, Iodium – Greed in Eating, Lycopodium Clavatum – Excessive Appetite, Morgan Gaertner – Sugar Craving, Oxytocin – Carbohydrate Craving, Pantothenic Acid – Fat Craving, Phosphorus – Fasting Fatigue, Rhodiola – Carbohydrate Craving, Serotonin (Hydrochloride) – Sugar Craving, Stomach (Suis) – Excessive Appetite, Thyroidinum (Suis) – Excessive Appetite

USES:

• For the temporary relief of symptoms including:

• fasting fatigue • greed in eating

• excessive appetite • sugar craving

• carbohydrate craving

• fat craving

These statements are based upon homeopathic principles. They have not been reviewed by the Food and Drug Administration.

WARNINGS:

If pregnant or breast-feeding, ask a health professional before use.

Keep out of reach of children. In case of overdose, contact a physician or Poison Control Center right away.

Tamper Evident: Sealed for your protection.

Do not use if seal is broken or missing.

KEEP OUT OF REACH OF CHILDREN:

In case of overdose, contact a physician or Poison Control Center right away.

DIRECTIONS:

3-10 drops under the tongue, 3 times a day or as directed by a health professional. Consult a physician for use in children under 12 years of age.

INACTIVE INGREDIENTS:

Demineralized water, 25% ethanol

QUESTIONS:

Dist. By: Deseret Biologicals, Inc.

469 W. Parkland Drive

Sandy, UT 84070

www.desbio.com

800-827-8204

PACKAGE LABEL DISPLAY:

DesBio

Appetite Control

Homeopathic
NDC 43742-2144-1

1 FL OZ (30 ml)